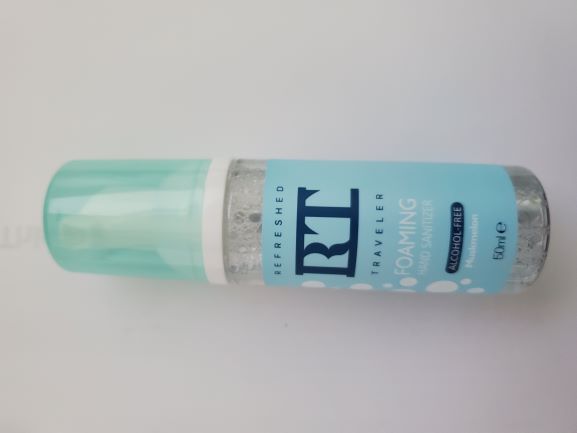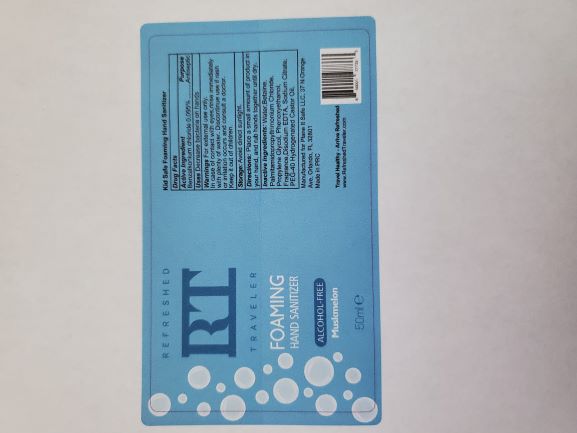 DRUG LABEL: Refreshed Traveler Foaming Hand Sanitizer
NDC: 72920-2014 | Form: LIQUID
Manufacturer: Plane It Safe LLC
Category: otc | Type: HUMAN OTC DRUG LABEL
Date: 20200829

ACTIVE INGREDIENTS: BENZETHONIUM CHLORIDE 50 mg/50 mL
INACTIVE INGREDIENTS: WATER

Refreshed Traveler Foaming Hand Sanitizer

INACTIVE INGREDIENT

Water,Betaine, Palmitamidopropyltrimonium Chloride, Propylene Glycol, Phenoxyethanol, Fragrance,Disodium EDTA, Sodium Citrate, PEG-40 Hydrogenated Castor Oil.

ACTIVE INGREDIENT

Benzalkonium chloride

Directions

Place a small amount of product inside the palm of your hand and gently rub together until dry

INDICATIONS AND USAGE

Decreases bacteria on hands

KEEP OUT OF REACH OF CHILDREN

For external use only. In case of contact with eyes rinse immediately with plenty of water. If rash or irritation consult a doctor. Keep out of the reach of children.

WARNINGS

For external use only. In case of contact with eyes rinse immediately with plenty of water. If rash or irritation consult a doctor. Keep out of the reach of children.

PURPOSE

Decrease the bacteria on hands

PACKAGE LABEL

Foaming Hand Sanitizer - Alcohol Free